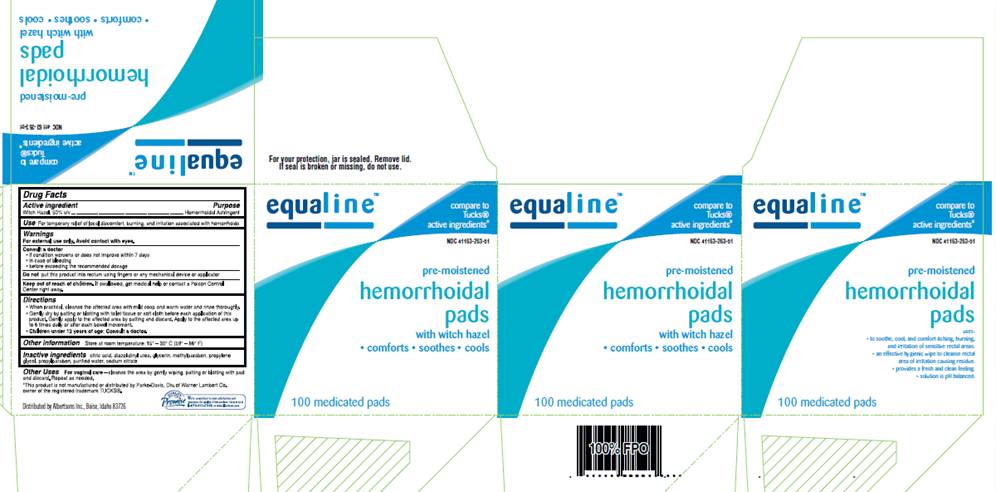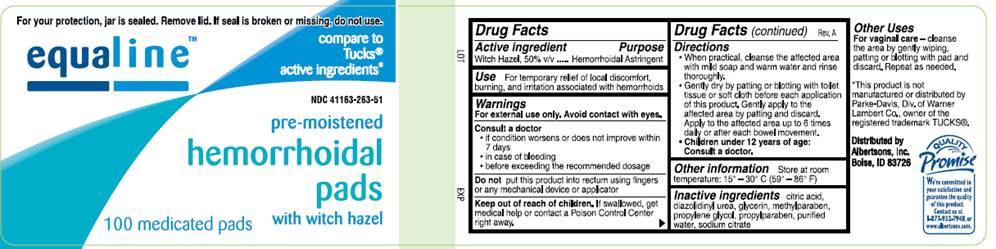 DRUG LABEL: Pre-moistened Hemorrhoidal Pads
NDC: 41163-263 | Form: SOLUTION
Manufacturer: Supervalu Inc
Category: otc | Type: HUMAN OTC DRUG LABEL
Date: 20100202

ACTIVE INGREDIENTS: witch hazel 0.50 mL/1 mL
INACTIVE INGREDIENTS: citric acid monohydrate; diazolidinylurea; glycerin; methylparaben; propylene glycol; propylparaben; sodium citrate; water

DRUG FACTS

ACTIVE INGREDIENT

Witch Hazel 50% v/v

PURPOSE

Hemorrhoidal Astringent

USE

For temporary relief of local discomfort, burning, and irritation associated with hemorrhoids

WARNINGS

For external use only. Avoid contact with eyes.

Consult a doctor

- if condition worsens or does not improve within 7 days
- in case of bleeding
- before exceeding the recommended dosage

Do not

put this product into rectum using fingers or any mechanical device or applicator

Keep out of reach of children

If swallowed, get medical help or contact a Poison Control Center right away.

DIRECTIONS

- When practical, cleanse the affected area with mild soap and warm water and rinse thoroughly.
- Gently dry by patting or blotting with toilet tissue or soft cloth before each application of this product. Gently apply to the affected area by patting and then discard. Apply to the affected area up to 6 times daily or after each bowel movement.
- Children under 12 years of age: consult a doctor.

OTHER INFORMATION

Store at room temperature: 15°- 30° C (59° - 86° F)

OTHER USES

For vaginal care - cleanse the area by gently wiping, patting or blotting with pad and discard. Repeat as needed.

INACTIVE INGREDIENTS

citric acid, diazolidinyl urea, glycerin, methylparaben, propylene glycol, propylparaben, purified water, sodium citrate

PACKAGE INFORMATION - 100 COUNT JAR This package is a representation. Packaging is similar for other sizes available.

For your protection, jar is sealed. Remove lid. If seal is broken or missing, do not use.

Equaline

Compare to Tucks® active ingredients*

NDC 41163-263-51
pre-moistened
hemorrhoidal pads
with witch hazel

100 medicated pads

Distributed by
Albertsons, Inc.
Boise, Idaho 83726

*This product is not manufactured or distributed by Parke-Davis, Div. of Warner Lambert Co., owner of the registered trademark TUCKS®.

We're committed to your satisfaction and guarantee the quality of this product. Contact us at 1/877-932-7948, or www.albertsons.com

PACKAGE INFORMATION - 100 COUNT CARTON This package is a representation. Packaging is similar for other sizes available.

For your protection, jar is sealed. Remove lid. If seal is broken or missing, do not use.

Compare to Tucks® active ingredients*
NDC 41163-263-51
pre-moistened
hemorrhoidal pads
with witch hazel
comforts - soothes - cools
uses:
* to soothe, cool, and comfort itching, burning, and irritation of sensitive rectal areas.
* an effective hygiene wipe to cleanse rectal area of irritation causing residue
* provides a fresh and clean feeling
* solution is pH balanced
100 medicated pads

Distributed by
Albertsons, Inc.
Boise, Idaho 83726
*This product is not manufactured or distributed by Parke-Davis, Div. of Warner Lambert Co., owner of the registered trademark TUCKS®.
We're committed to your satisfaction and guarantee the quality of this product. Contact us at 1/877-932-7948, or www.albertsons.com